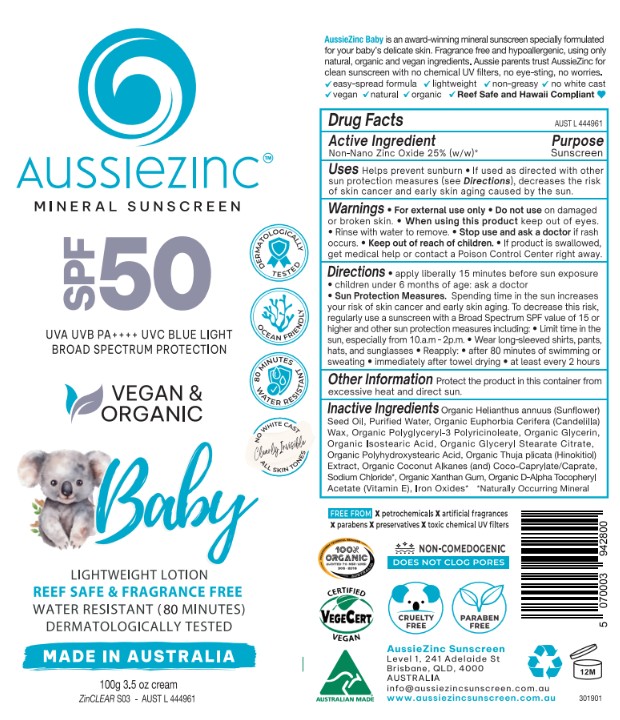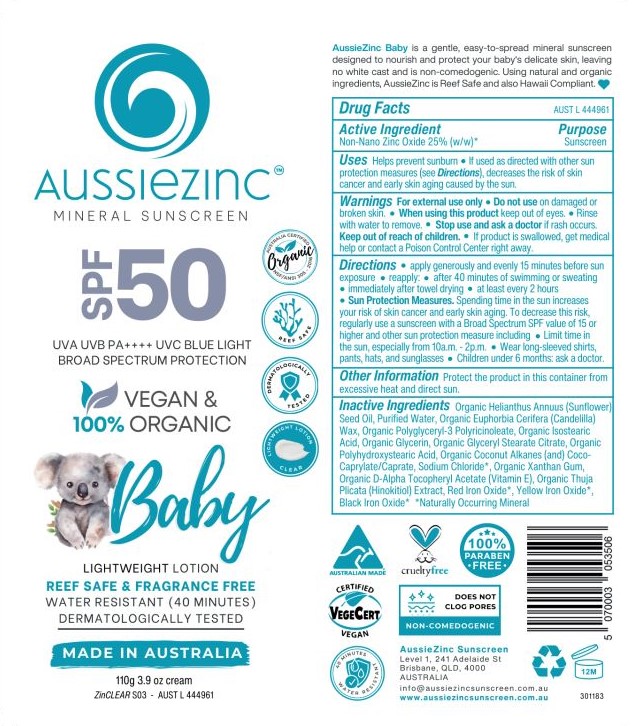 DRUG LABEL: Aussiezinc Mineral Sunscreen SPF50 Baby
NDC: 83252-056 | Form: CREAM
Manufacturer: Veganic SKN Limited
Category: otc | Type: HUMAN OTC DRUG LABEL
Date: 20251023

ACTIVE INGREDIENTS: ZINC OXIDE 25 kg/100 kg
INACTIVE INGREDIENTS: COCO-CAPRYLATE/CAPRATE; GLYCERYL STEARATE CITRATE; SODIUM HINOKITIOL; WATER; POLYHYDROXYSTEARIC ACID (2300 MW); SODIUM CHLORIDE; FERRIC OXIDE RED; CANDELILLA WAX; ISOSTEARIC ACID; GLYCERIN; SUNFLOWER OIL; FERRIC OXIDE YELLOW; POLYGLYCERYL-3 RICINOLEATE; XANTHAN GUM; FERROSOFERRIC OXIDE; ALPHA-TOCOPHEROL ACETATE; COCONUT ALKANES

Aussiezinc Mineral Sunscreen SPF50 Baby

Active ingredient: Zinc oxide 25% w/w

Purpose: sunscreen

INDICATIONS AND USAGE

Please kindly refer to label

WARNINGS

For external use only.
Do not use on damaged r broken skin.
When using this product keep out of eyes. Rinse with water to remove. Stop use and ask a
doctor if rash occurs.
Keep out of reach of children.
If product is swallowed, get medical help or contact a Poison Control Center right away

Keep out of reach of children

DOSAGE AND ADMINISTRATION

Please kindly refer to label.

INACTIVE INGREDIENT

Please kindly refer to label